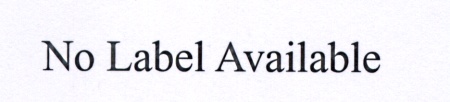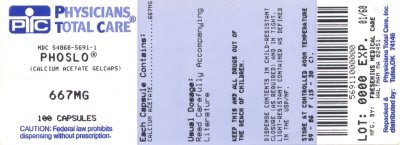 DRUG LABEL: Phoslo
NDC: 54868-5691 | Form: CAPSULE
Manufacturer: Physicians Total Care, Inc.
Category: prescription | Type: HUMAN PRESCRIPTION DRUG LABEL
Date: 20100310

ACTIVE INGREDIENTS: CALCIUM ACETATE 667 mg/1 1
INACTIVE INGREDIENTS: POLYETHYLENE GLYCOL 8000; FD&C BLUE NO. 1; D&C RED NO. 28; TITANIUM DIOXIDE; GELATIN

DESCRIPTION

Each opaque gelcap with a blue cap and white body is spin printed in blue and white ink with “PhosLo®” printed on the cap and “667 mg” printed on the body. Each gelcap contains 667 mg calcium acetate, USP (anhydrous; Ca(CH3COO)2; MW=158.17 grams) equal to 169 mg (8.45 mEq) calcium, and 10 mg of the inert binder, polyethylene glycol 8000 NF. The gelatin cap and body have the following inactive ingredients: FD&C blue #1, D&C red #28, titanium dioxide, USP and gelatin, USP.

PhosLo Gelcaps (calcium acetate) are administered orally for the control of hyperphosphatemia in end stage renal failure.

CLINICAL PHARMACOLOGY

Patients with advanced renal insufficiency (creatinine clearance less than 30 ml/min) exhibit phosphate retention and some degree of hyperphosphatemia. The retention of phosphate plays a pivotal role in causing secondary hyperparathyroidism associated with osteodystrophy, and soft-tissue calcification. The mechanism by which phosphate retention leads to hyperparathyroidism is not clearly delineated. Therapeutic efforts directed toward the control of hyperphosphatemia include reduction in the dietary intake of phosphate, inhibition of absorption of phosphate in the intestine with phosphate binders, and removal of phosphate from the body by more efficient methods of dialysis. The rate of removal of phosphate by dietary manipulation or by dialysis is insufficient. Dialysis patients absorb 40% to 80% of dietary phosphorus. Therefore, the fraction of dietary phosphate absorbed from the diet needs to be reduced by using phosphate binders in most renal failure patients on maintenance dialysis. Calcium acetate (PhosLo) when taken with meals, combines with dietary phosphate to form insoluble calcium phosphate which is excreted in the feces. Maintenance of serum phosphorus below 6.0 mg/dl is generally considered as a clinically acceptable outcome of treatment with phosphate binders. PhosLo is highly soluble at neutral pH, making the calcium readily available for binding to phosphate in the proximal small intestine.

Orally administered calcium acetate from pharmaceutical dosage forms has been demonstrated to be systemically absorbed up to approximately 40% under fasting conditions and up to approximately 30% under nonfasting conditions. This range represents data from both healthy subjects and renal dialysis patients under various conditions.

INDICATIONS AND USAGE

PhosLo is indicated for the control of hyperphosphatemia in end stage renal failure and does not promote aluminum absorption.

CONTRAINDICATIONS

Patients with hypercalcemia.

WARNINGS

Patients with end stage renal failure may develop hypercalcemia when given calcium with meals. No other calcium supplements should be given concurrently with PhosLo.

Progressive hypercalcemia due to overdose of PhosLo may be severe as to require emergency measures. Chronic hypercalcemia may lead to vascular calcification, and other soft-tissue calcification. The serum calcium level should be monitored twice weekly during the early dose adjustment period. The serum calcium times phosphate(CaXP) product should not be allowed to exceed 66. Radiographic evaluation of suspect anatomical region may be helpful in early detection of soft tissue calcification.

PRECAUTIONS

General

Excessive dosage of PhosLo induces hypercalcemia; therefore, early in the treatment during dosage adjustment serum calcium should be determined twice weekly. Should hypercalcemia develop, the dosage should be reduced or the treatment discontinued immediately depending on the severity of hypercalcemia. PhosLo should not be given to patients on digitalis, because hypercalcemia may precipitate cardiac arrhythmias. PhosLo therapy should always be started at low dose and should not be increased without careful monitoring of serum calcium. An estimate of daily calcium intake should be made initially and the intake adjusted as needed. Serum phosphorus should also be determined periodically.

Information for the Patient

The patient should be informed about compliance with dosage instructions, adherence to instructions about diet and avoidance of the use of nonprescription antacids. Patients should be informed about the symptoms of hypercalcemia (see ADVERSE REACTIONS section).

Drug Interactions

PhosLo may decrease the bioavailability of tetracyclines.

Carcinogenesis, Mutagenesis, Impairment of Fertility

Long term animal studies have not been performed to evaluate the carcinogenic potential, mutagenicity, or effect on fertility of PhosLo.

Pregnancy

Teratogenic Effects: Category C. Animal reproduction studies have not been conducted with PhosLo. It is not known whether PhosLo can cause fetal harm when administered to a pregnant woman or can affect reproduction capacity. PhosLo should be given to a pregnant woman only if clearly needed.

Pediatric Use

Safety and effectiveness in pediatric patients have not been established.

Geriatric Use

Of the total number of subjects in clinical studies of PhosLo (n=91), 25 percent were 65 and over, while 7 percent were 75 and over. No overall differences in safety or effectiveness were observed between these subjects and younger subjects, and other reported clinical experience has not identified differences in responses between the elderly and younger patients, but greater sensitivity of some older individuals cannot be ruled out.

ADVERSE REACTIONS

In clinical studies, patients have occasionally experienced nausea during PhosLo therapy. Hypercalcemia may occur during treatment with PhosLo. Mild hypercalcemia (Ca>10.5mg/dl) may be asymptomatic or manifest itself as constipation, anorexia, nausea and vomiting. More severe hypercalcemia (Ca>12mg/dl) is associated with confusion, delirium, stupor and coma. Mild hypercalcemia is easily controlled by reducing the PhosLo dose or temporarily discontinuing therapy. Severe hypercalcemia can be treated by acute hemodialysis and discontinuing PhosLo therapy. Decreasing dialysate calcium concentration could reduce the incidence and severity of PhosLo induced hypercalcemia. The long-term effect of PhosLo on the progression of vascular or soft tissue calcification has not been determined.

Isolated cases of pruritus have been reported which may represent allergic reactions.

OVERDOSAGE

Administration of PhosLo in excess of the appropriate daily dosage can cause severe hypercalcemia (see ADVERSE REACTIONS section).

DOSAGE AND ADMINISTRATION

The recommended initial dose of PhosLo for the adult dialysis patient is 2 gelcaps with each meal. The dosage may be increased gradually to bring the serum phosphate value below 6 mg/dl, as long as hypercalcemia does not develop. Most patients require 3-4 gelcaps with each meal.

HOW SUPPLIED

Gelcap: A white and blue gelcap for oral administration containing 667 mg calcium acetate (anhydrous Ca(CH3COO)2; MW=158.17 grams) equal to 169 mg (8.45 mEq) calcium.

Gelcap

NDC 54868-5691-0 Bottles of 200

NDC 54868-5691-1 Bottles of 100

STORAGE

Store at 25°C (77°F); excursions permitted to 15-30°C (59-86°F). See USP “Controlled Room Temperature.”

Rx only

Manufactured for
Fresenius Medical Care
Waltham, MA 02451

100623.00 01/07

Repackaging and Relabeling by:
Physicians Total Care, Inc.
Tulsa, OK 74146

PRINCIPAL DISPLAY PANEL

PhosLo Gelcaps (calcium acetate)

NDC 54868-5691

667 mg Gelcap

NDC 54868-3460